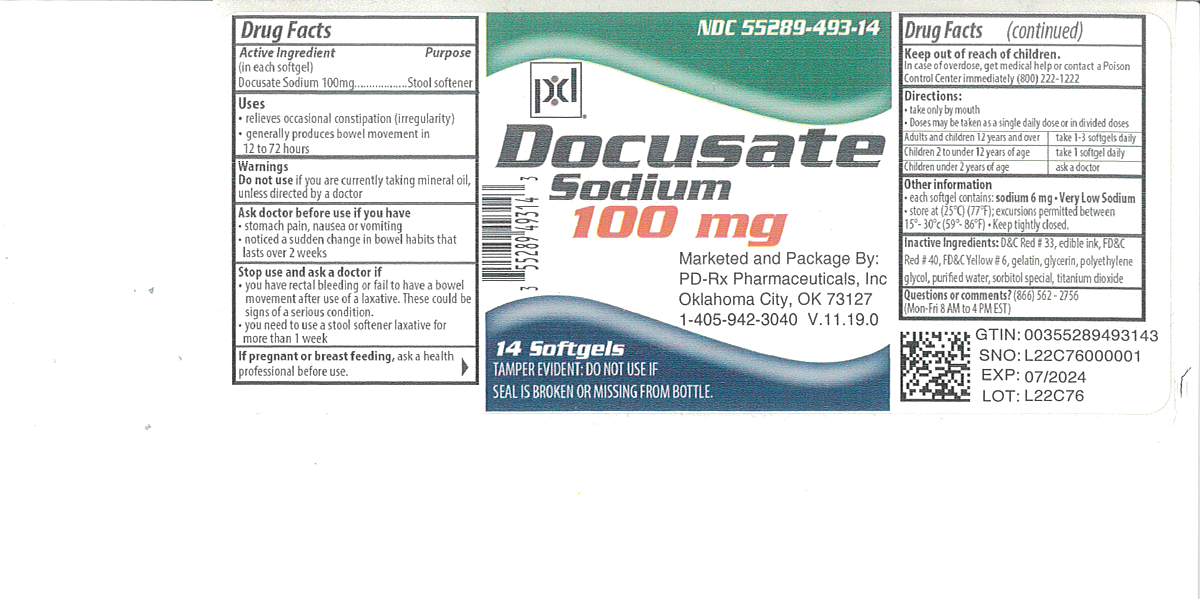 DRUG LABEL: Docusate Sodium
NDC: 55289-493 | Form: CAPSULE
Manufacturer: PD-Rx Pharmaceuticals, Inc.
Category: otc | Type: HUMAN OTC DRUG LABEL
Date: 20251020

ACTIVE INGREDIENTS: DOCUSATE SODIUM 100 mg/1 1
INACTIVE INGREDIENTS: FD&C RED NO. 40; FD&C YELLOW NO. 6; GELATIN, UNSPECIFIED; GLYCERIN; POLYETHYLENE GLYCOL, UNSPECIFIED; WATER; SORBITOL; TITANIUM DIOXIDE; D&C RED NO. 33

Docusate Sodium 100 mg Softgels

Active ingredient (in each softgel)

Docusate Sodium 100 mg

Purpose

Stool softener

Uses

- relieves occasional constipation (irregularity)
- generally produces bowel movement in 12 to 72 hours

Warnings

Do not use if you are presently taking mineral oil, unless directed by a doctor

Ask a doctor before use if you have

- stomach pain
- nausea or vomiting
- noticed a sudden change in bowel habits that lasts over 2 weeks

Stop use and ask a doctor if

- you have rectal bleeding or fail to have bowel movement after use of a laxative. These could be signs of a serious condition.
- you need to use a stool softener laxative for more than 1 week

If pregnant or breast-feeding,

ask a health professional before use.

Keep out of reach of children.

In case of overdose, get medical help or contact a Poison Control Center right away. (1-800-222-1222)

Directions

- Take only by mouth. Doses may be taken as a single daily dose or in divided doses.

adults and children 12 years and over | take 1-3 softgels daily
children 2 to under 12 years of age | take 1 softgel daily
children under 2 years of age | ask a doctor

Other information

- Tamper Evident: Do not use if seal is broken or missing from bottle
- each softgel contains: sodium 6 mg
- VERY LOW SODIUM
- store at 25oC (77oF); excursions permitted between 15o-30oC (59o-86oF).

keep tightly closed.

Inactive ingredients

D&C Red #33, edible ink, FD&C Red #40, FD&C Yellow #6, gelatin, glycerin, polyethylene glycol, purified water, sorbitol special

Questions?

Adverse drug event call:(866) 562-2756 Mon-Fri 8 AM to 4 PM

PACKAGE LABEL

Docusate

Sodium